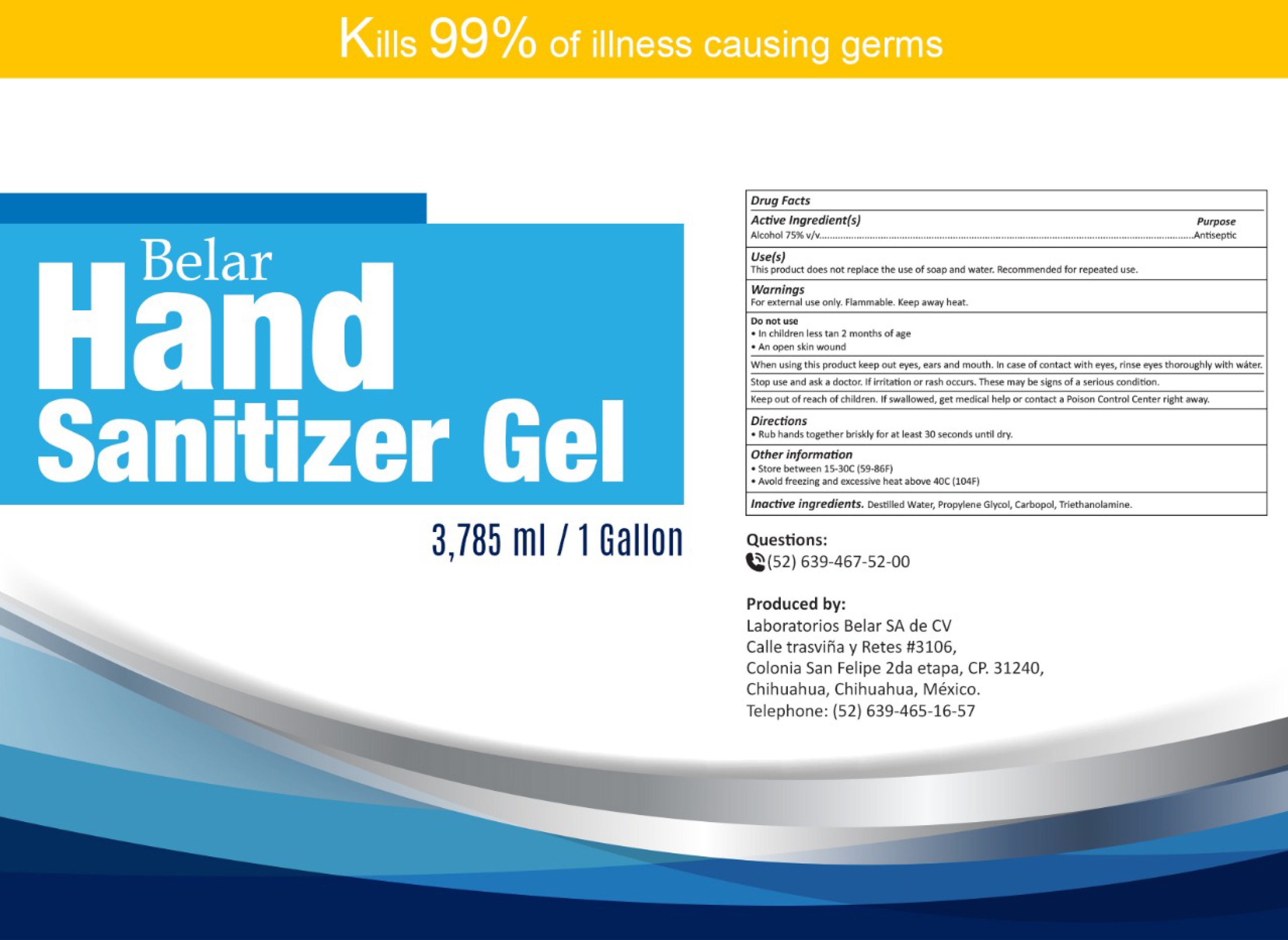 DRUG LABEL: Belar Hand Sanitizer
NDC: 79716-001 | Form: GEL
Manufacturer: Laboratorios Belar S.A. De C.V.
Category: otc | Type: HUMAN OTC DRUG LABEL
Date: 20220106

ACTIVE INGREDIENTS: ALCOHOL 0.75 mL/1 mL
INACTIVE INGREDIENTS: WATER; PROPYLENE GLYCOL; CARBOMER HOMOPOLYMER, UNSPECIFIED TYPE; TROLAMINE

Belar Hand Sanitizer Gel

Active Ingredient(s)

Alcohol 75% v/v

Purpose

Antiseptic

Use(s)

This product does not replace the use of soap and water, Recommended for repeated use.

Warnings

For external use only. Flammable. Keep away heat.

Do not use

- In children less tan 2 months of age
- An open skin wound

When using this product

keep out eyes, ears and mouth. In case of contact with eyes, rinse eyes thoroughly with water.

Stop use and ask a doctor.

if irritation or rash occurs. These may be signs of a serious condition.

Keep out of reach of children.

If swallowed, get medical help or contact a Poison Control Center right away.

Directions

- Rub hands together briskly for at least 30 seconds until dry.

Other information

- Store between 15-30C (59-86F)
- Avoid freezing and excessive heat above 40C (104F)

Inactive ingredients:

Distilled Water, Propylene Glycol, Carbopol, Triethanolamine.